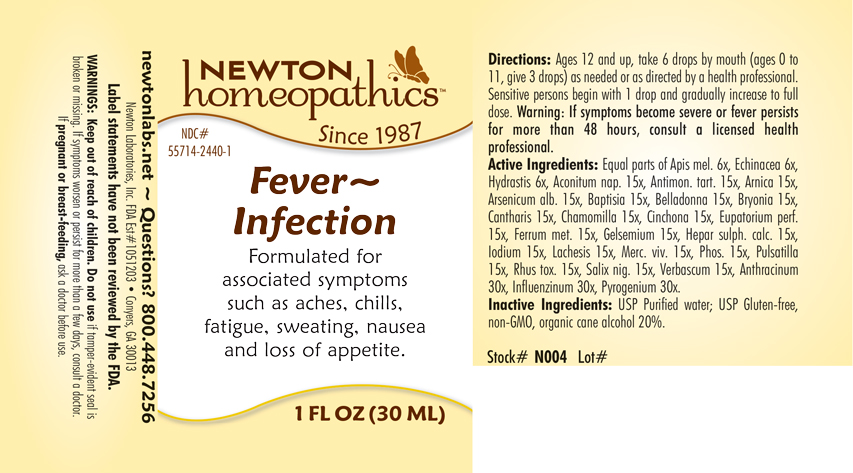 DRUG LABEL: Fever - Infection
NDC: 55714-2440 | Form: LIQUID
Manufacturer: Newton Laboratories, Inc.
Category: homeopathic | Type: HUMAN OTC DRUG LABEL
Date: 20250206

ACTIVE INGREDIENTS: BACILLUS ANTHRACIS IMMUNOSERUM RABBIT 30 [hp_X]/1 mL; INFLUENZA A VIRUS 30 [hp_X]/1 mL; RANCID BEEF 30 [hp_X]/1 mL; ACONITUM NAPELLUS 15 [hp_X]/1 mL; ANTIMONY POTASSIUM TARTRATE 15 [hp_X]/1 mL; ARNICA MONTANA 15 [hp_X]/1 mL; ARSENIC TRIOXIDE 15 [hp_X]/1 mL; BAPTISIA TINCTORIA 15 [hp_X]/1 mL; ATROPA BELLADONNA 15 [hp_X]/1 mL; BRYONIA ALBA ROOT 15 [hp_X]/1 mL; LYTTA VESICATORIA 15 [hp_X]/1 mL; MATRICARIA RECUTITA 15 [hp_X]/1 mL; CINCHONA OFFICINALIS BARK 15 [hp_X]/1 mL; EUPATORIUM PERFOLIATUM FLOWERING TOP 15 [hp_X]/1 mL; IRON 15 [hp_X]/1 mL; GELSEMIUM SEMPERVIRENS ROOT 15 [hp_X]/1 mL; CALCIUM SULFIDE 15 [hp_X]/1 mL; IODINE 15 [hp_X]/1 mL; LACHESIS MUTA VENOM 15 [hp_X]/1 mL; MERCURY 15 [hp_X]/1 mL; PHOSPHORUS 15 [hp_X]/1 mL; PULSATILLA VULGARIS 15 [hp_X]/1 mL; TOXICODENDRON PUBESCENS LEAF 15 [hp_X]/1 mL; SALIX NIGRA BARK 15 [hp_X]/1 mL; VERBASCUM THAPSUS 15 [hp_X]/1 mL; APIS MELLIFERA 6 [hp_X]/1 mL; ECHINACEA, UNSPECIFIED 6 [hp_X]/1 mL; GOLDENSEAL 6 [hp_X]/1 mL; INFLUENZA B VIRUS 30 [hp_X]/1 mL
INACTIVE INGREDIENTS: WATER; ALCOHOL

Fever 2440L

INDICATIONS & USAGE SECTION

Formulated for associated symptoms such as aches, chills, fatigue, sweating, nausea and loss of appetite.

DOSAGE & ADMINISTRATION SECTION

Directions: Ages 12 and up, take 6 drops by mouth (ages 0 to 11, give 3 drops) as needed or as directed by a health professional. Sensitive persons begin with 1 drop and gradually increase to full dose. Warning: If symptoms become severe or fever persists for more than 48 hours, consult a licensed health professional.

OTC - ACTIVE INGREDIENT SECTION

Equal parts of Apis mel. 6x, Echinacea 6x, Hydrastis 6x, Aconitum nap. 15x, Antimon. tart. 15x, Arnica 15x, Arsenicum alb. 15x, Baptisia 15x, Belladonna 15x, Bryonia 15x, Cantharis 15x, Chamomilla 15x, Cinchona 15x, Eupatorium perf. 15x, Ferrum metallicum 15x, Gelsemium 15x, Hepar sulph.calc. 15x, Iodium 15x, Lachesis 15x, Merc. viv. 15x, Phosphorus 15x, Pulsatilla 15x, Rhus toxicodendron 15x, Salix nigra 15x, Verbascum 15x, Anthracinum 30x, Influenzinum 30x, Pyrogenium 30x.

OTC - PURPOSE SECTION

Formulated for associated symptoms such as aches, chills, fatigue, sweating, nausea and loss of appetite.

INACTIVE INGREDIENT SECTION

Inactive Ingredients: USP Purified water; USP Gluten-free, non-GMO, organic cane alcohol 20%.

WARNINGS SECTION

WARNINGS: Keep out of reach of children. Do not use if tamper-evident seal is broken or missing. If symptoms worsen or persist for more than a few days, consult a doctor. If pregnant or breast-feeding, ask a doctor before use.

QUESTIONS SECTION

newtonlabs.net - Questions? 800.448.7256

Newton Laboratories, Inc. FDA Est # 1051203 - Conyers, GA 30013

OTC - PREGNANCY OR BREAST FEEDING SECTION

If pregnant or breast-feeding, ask a doctor before use.

OTC - KEEP OUT OF REACH OF CHILDREN SECTION

Keep out of reach of children